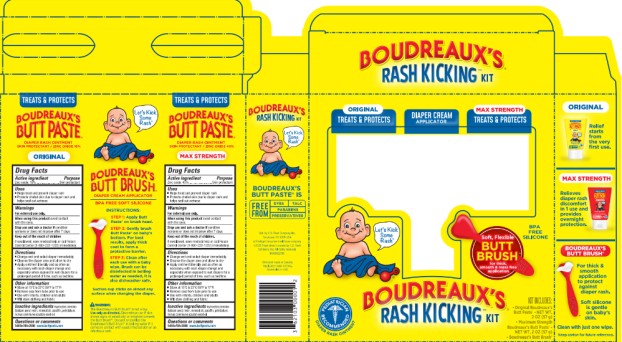 DRUG LABEL: Boudreauxs Rash Kicking Kit
NDC: 0132-0325 | Form: KIT | Route: TOPICAL
Manufacturer: C.B. Fleet Company, Inc.
Category: otc | Type: HUMAN OTC DRUG LABEL
Date: 20251027

ACTIVE INGREDIENTS: ZINC OXIDE 16 g/57 g; ZINC OXIDE 40 g/57 g
INACTIVE INGREDIENTS: BALSAM PERU; CASTOR OIL; MINERAL OIL; PARAFFIN; PETROLATUM; BALSAM PERU; CASTOR OIL; MINERAL OIL; PARAFFIN; PETROLATUM

Boudreauxs Complete Rash Kit - Orig-Max_0132-0325

ORIGINAL BOUDREAUX’S BUTT PASTE ®

DIAPER RASH OINTMENT

SKIN PROTECTANT (ZINC OXIDE)

Drug Facts

Active ingredient

Zinc oxide, 16%

Purpose

Skin protectant

Uses

- Helps treat and prevent diaper rash
- Protects chafed skin due to diaper rash and helps seal out wetness

Warnings

For external use only

When using this product

avoid contact with the eyes

Stop use and ask a doctor if

condition worsens or does not improve after 7 days

Keep out of the reach of children

If swallowed, seek medical help or call Poison Control Center (1-800-222-1222) immediately

Directions

- Change wet and soiled diaper immediately
- Cleanse the diaper area and allow to dry
- Apply ointment liberally and as often as necessary with each diaper change and especially when exposed to wet diapers for a prolonged period of time, such as bedtime

Other information

- Store at 15°C to 25°C (59°F to 77°F)
- Remove seal from tube prior to use
- Use with infants, children and adults
- Will stain clothing and fabric

Inactive ingredients

myroxylon pereiraie (balsam peru) resin, mineral oil, paraffin, petrolatum, ricinus communis (castor) seed oil

Questions or comments

1-855-785-2888 www.buttpaste.com

MAX STRENGTH BOUDREAUX’S BUTT PASTE ®

DIAPER RASH OINTMENT

SKIN PROTECTANT (ZINC OXIDE)

Drug Facts

Active ingredient

Zinc oxide, 40%

Purpose

Skin protectant

Uses

- Helps treat and prevent diaper rash
- Protects chafed skin due to diaper rash and helps seal out wetness

Warnings

For external use only

When using this product

avoid contact with the eyes

Stop use and ask a doctor if

condition worsens or does not improve after 7 days

Keep out of the reach of children

If swallowed, seek medical help or call Poison Control Center (1-800-222-1222) immediately

Directions

- Change wet and soiled diaper immediately
- Cleanse the diaper area and allow to dry
- Apply ointment liberally and as often as necessary with each diaper change and especially when exposed to wet diapers for a prolonged period of time, such as bedtime

Other information

- Store at 15°C to 25°C (59°F to 77°F)
- Remove seal from tube prior to use
- Use with infants, children and adults
- Will stain clothing and fabric

Inactive ingredients

myroxylon pereiraie (balsam peru) resin, mineral oil, paraffin, petrolatum, ricinus communis (castor) seed oil

Questions or comments

1-855-785-2888 www.buttpaste.com

BOUDREAUX’S® BUTT BRUSH

DIAPER CREAM APPLICATOR

BPA FREE SILICONE

Instructions:

Step 1: Apply Butt Paste® on brush head.

Step 2: Gently brush Butt Paste® on baby’s bottom. For best results, apply thick coat to form a protective barrier.

Step 3: Clean after each use with a baby wipe. Brush can be disinfected in boiling water as needed. It is also dishwasher safe.

Suction cup sticks on almost any surface when changing the diaper.

WARNING:

The Boudreaux’s Butt Brush™ is not a toy. Use only as directed. Discontinue use if skin shows signs of sensitivity or irritation towards the Butt Brush™. Discard or sterilize the Boudreaux’s Butt Brush™ in boiling water if comes in contact with yeast infected skin or an infectious rash.

Principal display panel

BOUDREAUX’S® RASH KICKING™ KIT

KIT INCLUDES:

-Original Boudreaux’s Butt Paste®-NET WT. 2oz (57 g)

-Maximum Strength Boudreaux’s Butt Paste®- NET WT. 2oz (57 g)

-Boudreaux’s Butt Brush™